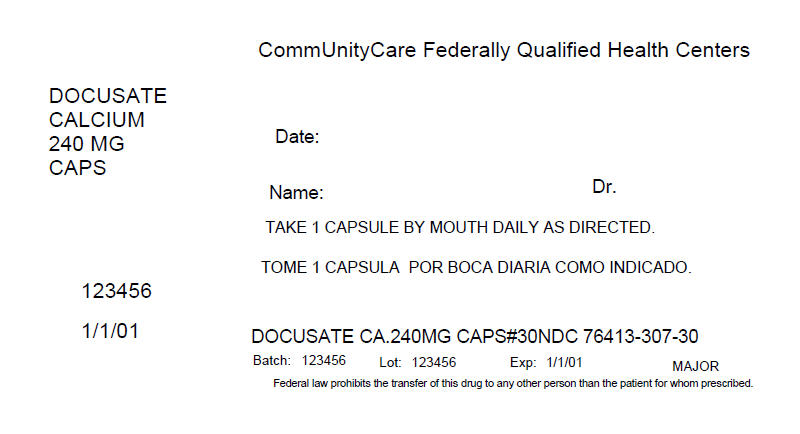 DRUG LABEL: Docusate calcium
NDC: 76413-307 | Form: CAPSULE, LIQUID FILLED
Manufacturer: Central Texas Community Health Centers
Category: otc | Type: HUMAN OTC DRUG LABEL
Date: 20160322

ACTIVE INGREDIENTS: Docusate calcium 240 mg/1 1
INACTIVE INGREDIENTS: CORN OIL; D&C RED NO. 33; FD&C RED NO. 40; GELATIN; GLYCERIN; WATER; SORBITOL

Docusate calcium

Active ingredient (in each softgel)

Docusate Calcium 240 mg

Purpose

Stool softener

Uses

for relief of occasional constipation. This product generally produces a bowel movement within 12 to 72 hours.

Warnings

Do not use

- if you are currently taking mineral oil, unless directed by a doctor
- when abdominal pain, nausea, or vomiting are present
- for longer than 1 week, unless directed by a doctor

Ask a doctor before use if

you notice a sudden change in bowel habits that persists over a period of 2 weeks.

Stop use and ask a doctor if

- you have rectal bleeding
- you fail to have a bowel movement after use

These could be signs of s serious condition.

If pregnant or breast-feeding,

ask a health care professional before use.

Keep out of reach of children.

In case of overdose, get medical help or contact a Poison Control Center right away.

Directions

- adults and children over 12 years of age: take 1 softgel daily for several days, or until bowel movements are normal, or as directed by a doctor
- children under 12 years of age: take as directed by a doctor

Other information

- store between 15º-30ºC (59º-86ºF)

Inactive ingredients

corn oil, D&C red #33, edible white ink, FD&C red #40, gelatin, glycerin, purified water and sorbitol special.

Questions or comments?

1-800-645-2158

Principal Display Panel

Compare to active ingredient in SURFAK®*

Safe, Effective, Non-Habit Forming

Stool Softener Laxative DC

Docusate Calcium USP, 240 mg

SOFTGEL CAPSULES

TAMPER EVIDENT: DO NOT USE IF IMPRINTED SAFETY SEAL UNDER CAP IS BROKEN OR MISSING

*Rugby Laboratories is not affiliated with the owner of the trademark Surfak®.

Distributed by: Rugby Laboratories

31778 Enterprise Drive

Livonia, MI 48150

www.rugbylaboratories.com

PRINCIPAL DISPLAY PANEL - 240 mg Capsule Bottle Label

CommUnityCare Federally Qualified Health Centers

DOCUSATE
CALCIUM
240 MG
CAPS

Date:

Name:
Dr.

TAKE 1 CAPSULE BY MOUTH DAILY AS DIRECTED.

123456

1/1/01

DOCUSATE CA.240MG CAPS#30NDC 76413-307-30

Batch: 123456
Lot: 123456
Exp: 1/1/01
MAJOR

Federal law prohibits the transfer of this drug to any other person than the patient for whom prescribed.